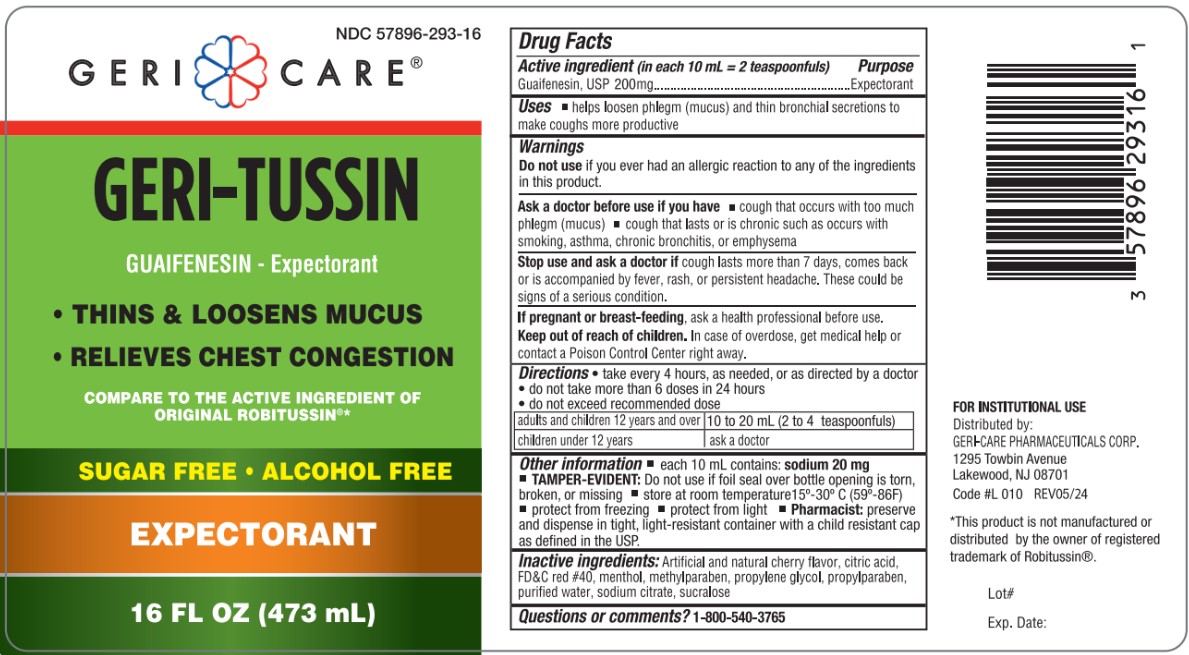 DRUG LABEL: Geri-Tussin
NDC: 57896-293 | Form: LIQUID
Manufacturer: Geri-Care Pharmaceuticals, Corp
Category: otc | Type: HUMAN OTC DRUG LABEL
Date: 20251211

ACTIVE INGREDIENTS: GUAIFENESIN 200 mg/10 mL
INACTIVE INGREDIENTS: ANHYDROUS CITRIC ACID; FD&C RED NO. 40; MENTHOL; METHYLPARABEN; PROPYLENE GLYCOL; PROPYLPARABEN; WATER; SODIUM CITRATE; SUCRALOSE

Geri-Care GERI-TUSSIN

ACTIVE INGREDIENT

in each 10 mL = 2 teaspoonfuls

Guaifenesin - 200 mg

Purpose

Expectorant

Uses

- helps loosen phlegm (mucus) and thin bronchial secretions to make coughs more productive

Warnings

Do not useif you have ever had an allergic reaction to any of the ingredients in this product.

Ask a doctor before use if you have

- cough with too much phlegm (mucus)
- cough that lasts or is chronic such as occurs with smoking, asthma, chronic bronchitis or emphysema

Stop use and ask a doctor if cough lasts more than 7 days, comes back or is accompanied by fever, rash, or headache that lasts. These could be signs of a serious condition.

PREGNANCY OR BREAST FEEDING

If pregnant or breast-feeding, ask a health professional before use.

Keep out of reach of children.In case of overdose, get medical help or contact a Poison Control Center right away.

Directions

- take every 4 hours, as needed, or as directed by a doctor
- do not take more than 6 doses in 24 hours
- do not exceed recommended dose

adults and children 12 years and over | 10 to 20 mL (2 to 4 teaspoonfuls)
children under 12 years | ask a doctor

Other information

- each 10 mL contains: sodium 20 mg
- TAMPER-EVIDENT: Do not use if foil seal over bottle opening is torn, broken or missing.
- store at room temperature 15°-30°C (59°-86°F)
- protect from freezing
- protect from light
- Pharmacist:Preserve and dispense in a tight, light resistant container with a child resistant cap as defined in the USP.

INACTIVE INGREDIENT

Inactive ingredients: Artificial and natural cherry flavor, citric acid, FD&C red #40, menthol, methylparaben, propylene glycol, propylparaben, purified water, sodium citrate, sucralose

Questions or comments?1-800-540-3765

PACKAGE LABEL

Geri Care®

GERI - TUSSIN

SUGAR FREE ♦ ALCOHOL FREE

EXPECTORANT

Distributed by: GERI-CARE PHARMACEUTICALS CORP.

1295 Towbin Avenue

Lakewood, NJ 08701

Code# L 010 REV05/24